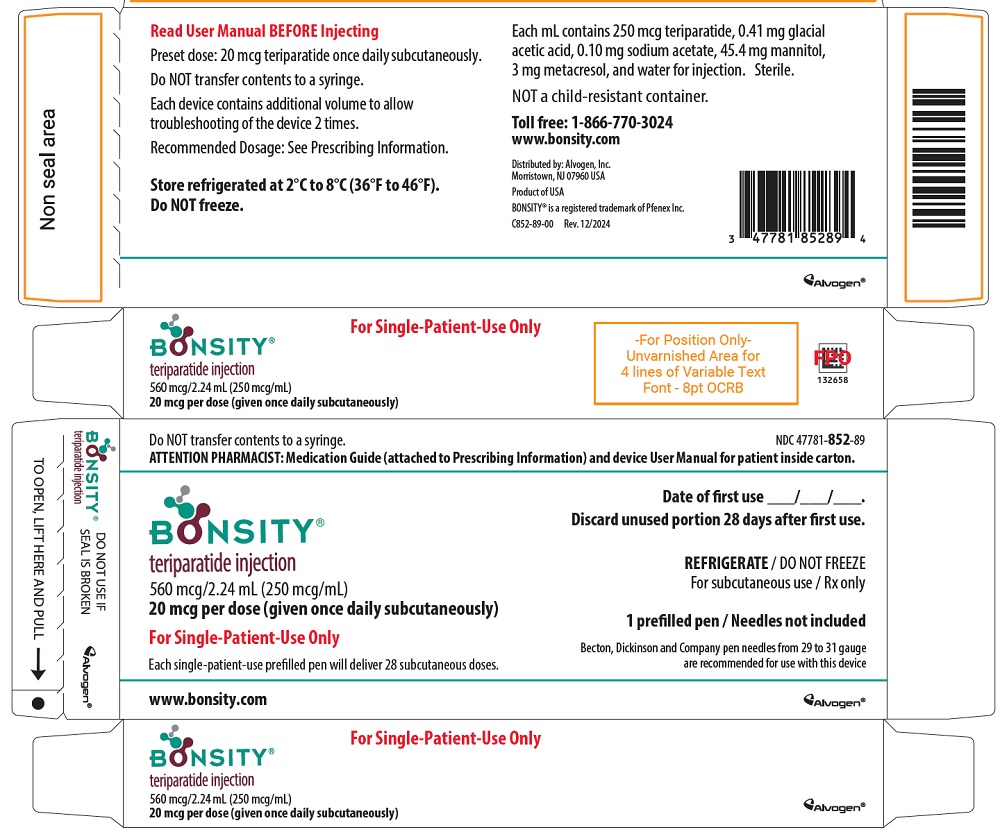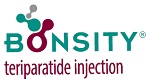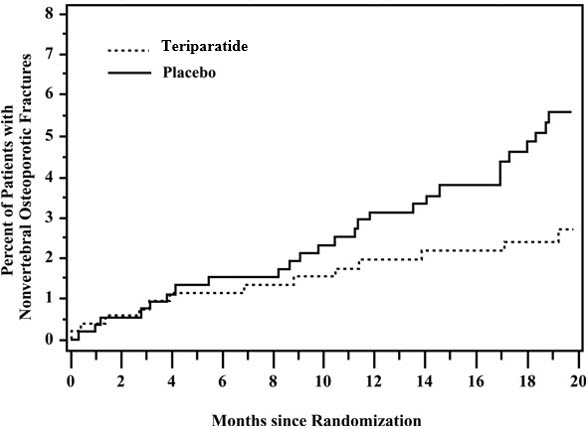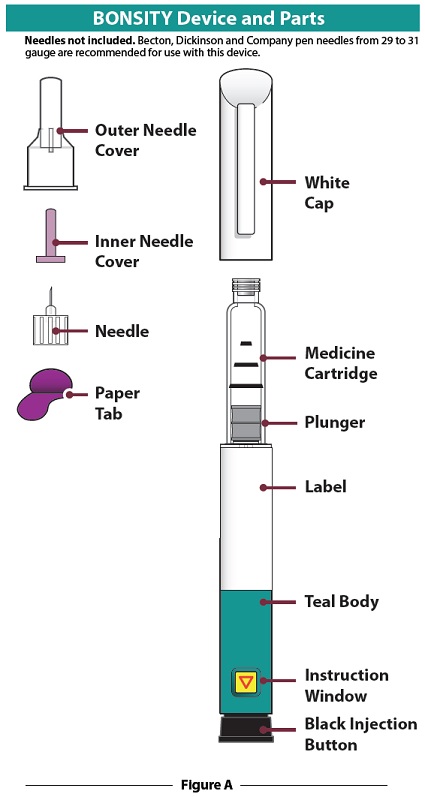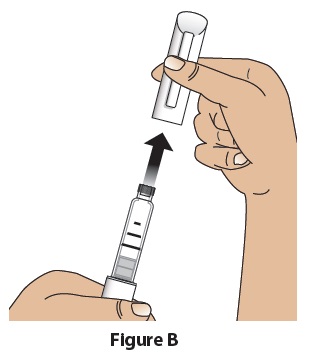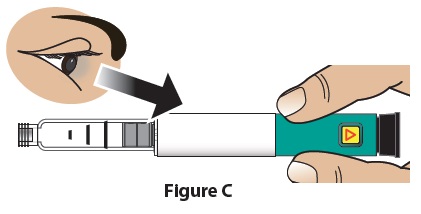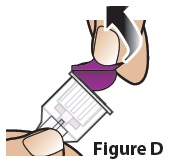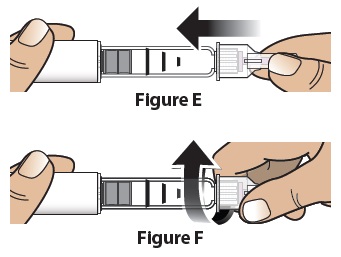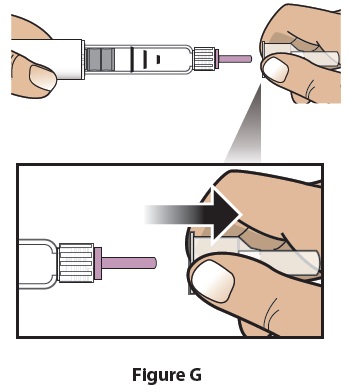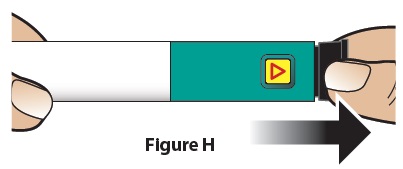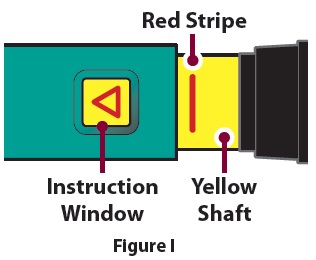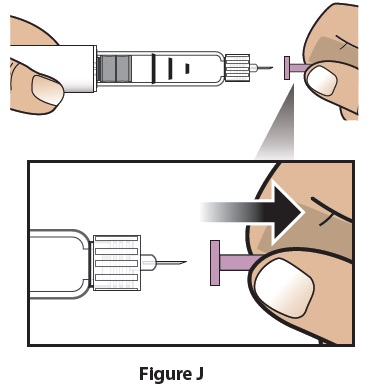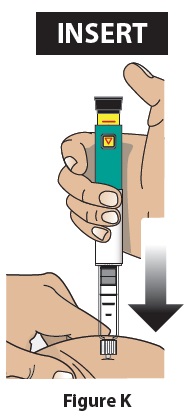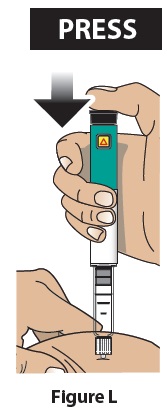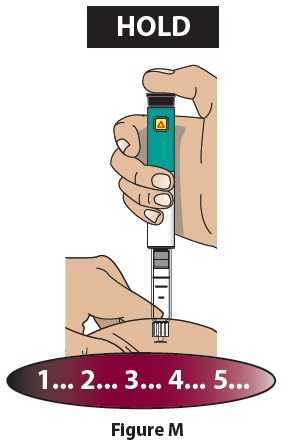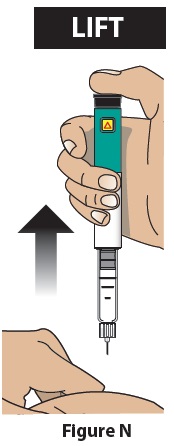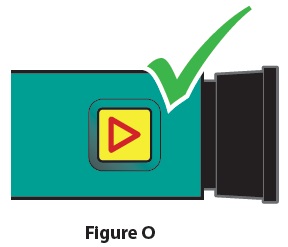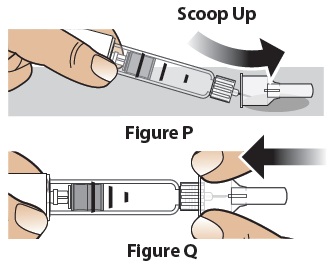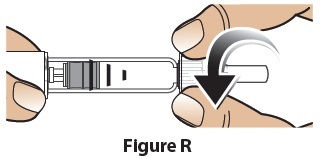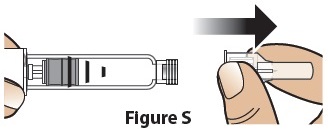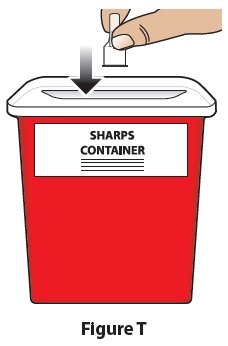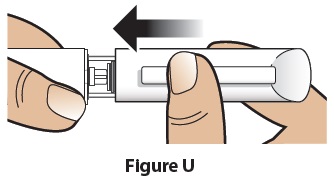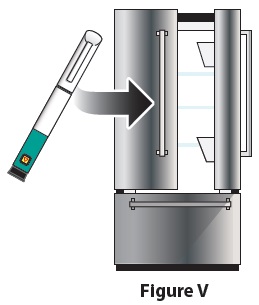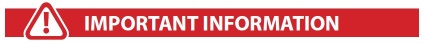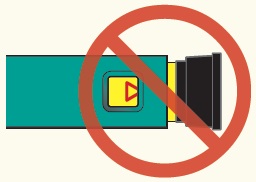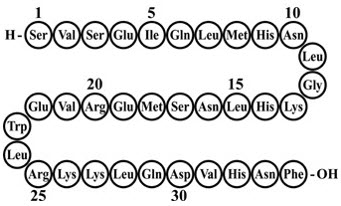 DRUG LABEL: Bonsity
NDC: 47781-852 | Form: INJECTION, SOLUTION
Manufacturer: Alvogen Inc.
Category: prescription | Type: HUMAN PRESCRIPTION DRUG LABEL
Date: 20250601

ACTIVE INGREDIENTS: TERIPARATIDE 250 ug/1 mL
INACTIVE INGREDIENTS: ACETIC ACID; SODIUM ACETATE; MANNITOL; METACRESOL; WATER

HIGHLIGHTS OF PRESCRIBING INFORMATION

These highlights do not include all the information needed to use BONSITY safely and effectively. See full prescribing information for BONSITY.
BONSITY (teriparatide injection), for subcutaneous use
Initial U.S. Approval: 1987

1 INDICATIONS AND USAGE

BONSITY is a parathyroid hormone analog, (PTH 1-34), indicated for:

- Treatment of postmenopausal women with osteoporosis at high risk for fracture or patients who have failed or are intolerant to other available osteoporosis therapy (1)
- Increase of bone mass in men with primary or hypogonadal osteoporosis at high risk for fracture or patients who have failed or are intolerant to other available osteoporosis therapy (1)
- Treatment of men and women with osteoporosis associated with sustained systemic glucocorticoid therapy at high risk for fracture or patients who have failed or are intolerant to other available osteoporosis therapy (1)

2 DOSAGE AND ADMINISTRATION

- Recommended dosage is 20 mcg subcutaneously once a day (2.1)
- Consider supplemental calcium and Vitamin D based on individual patient needs (2.1)
- Administer as a subcutaneous injection into the thigh or abdominal region (2.2)
- Administer initially under circumstances in which the patient can sit or lie down if symptoms of orthostatic hypotension occur (2.2)
- Use of teriparatide for more than 2 years during a patient's lifetime should only be considered if a patient remains at or has returned to having a high risk for fracture (2.3)

3 DOSAGE FORMS AND STRENGTHS

Injection: 560 mcg/2.24 mL (250 mcg/mL) in single-patient-use prefilled pen intended to deliver 28 daily doses of 20 mcg (3)

4 CONTRAINDICATIONS

- Patients with hypersensitivity to teriparatide or to any of its excipients (4)

5 WARNINGS AND PRECAUTIONS

- Osteosarcoma: Avoid use in patients with increased risk of osteosarcoma including patients with open epiphyses, metabolic bone diseases including Paget's disease, bone metastases or history of skeletal malignancies, prior external beam or implant radiation therapy involving the skeleton, and hereditary disorders predisposing to osteosarcoma. (5.1)
- Hypercalcemia and Cutaneous Calcification: Avoid in patients known to have an underlying hypercalcemic disorder. Discontinue in patients developing worsening of previously stable cutaneous calcification. (5.2)
- Risk of Urolithiasis: Consider the risk/benefit in patients with active or recent urolithiasis because of risk of exacerbation (5.3)
- Orthostatic Hypotension: Transient orthostatic hypotension may occur with initial doses of BONSITY (5.4)

6 ADVERSE REACTIONS

Most common adverse reactions (>10%) include: arthralgia, pain, and nausea (6.1)

To report SUSPECTED ADVERSE REACTIONS, contact Alvogen, Inc. at 1-866-770-3024 or FDA at 1-800-FDA-1088 or www.fda.gov/medwatch

7 DRUG INTERACTIONS

Digoxin: Transient hypercalcemia may predispose patients to digitalis toxicity (5.5, 7.1)

8 USE IN SPECIFIC POPULATIONS

- Pregnancy: Consider discontinuing when pregnancy is recognized (8.1)
- Lactation: Breastfeeding is not recommended (8.2)
- Pediatric Use: Safety and effectiveness not established. Avoid use due to increased baseline risk of osteosarcoma (5.1, 8.4)

FULL PRESCRIBING INFORMATION

1 INDICATIONS AND USAGE

BONSITY is indicated:

- For the treatment of postmenopausal women with osteoporosis at high risk for fracture (defined herein as having a history of osteoporotic fracture or multiple risk factors for fracture) or who have failed or are intolerant to other available osteoporosis therapy. In postmenopausal women with osteoporosis, BONSITY reduces the risk of vertebral and nonvertebral fractures.
- To increase bone mass in men with primary or hypogonadal osteoporosis at high risk for fracture or who have failed or are intolerant to other available osteoporosis therapy.
- For the treatment of men and women with osteoporosis associated with sustained systemic glucocorticoid therapy (daily dosage equivalent to 5 mg or greater of prednisone) at high risk for fracture or who have failed or are intolerant to other available osteoporosis therapy.

2 DOSAGE AND ADMINISTRATION

2.1 Recommended Dosage

The recommended dosage is 20 mcg given subcutaneously once a day. Instruct patients to take supplemental calcium and vitamin D if daily dietary intake is inadequate.

2.2 Administration Instructions

- Administer BONSITY as a subcutaneous injection into the thigh or abdominal region. BONSITY is not approved for intravenous or intramuscular use.
- BONSITY should be administered initially under circumstances in which the patient can sit or lie down if symptoms of orthostatic hypotension occur [see Warnings and Precautions (5.4)].
- Parenteral drug products should be inspected visually for particulate matter and discoloration prior to administration (BONSITY is a clear and colorless liquid). Do not use if solid particles appear or if the solution is cloudy or colored.
- Patients and/or caregivers who administer BONSITY should receive appropriate training and instruction on the proper use of the BONSITY delivery device from a qualified health professional.

2.3 Recommended Treatment Duration

Use of teriparatide for more than 2 years during a patient's lifetime should only be considered if a patient remains at or has returned to having a high risk for fracture [see Warnings and Precautions (5.1)].

3 DOSAGE FORMS AND STRENGTHS

Injection: 560 mcg/2.24 mL (250 mcg/mL)

Colorless solution in a single-patient-use prefilled pen intended to deliver 28 daily doses of 20 mcg.

4 CONTRAINDICATIONS

BONSITY is contraindicated in patients with hypersensitivity to teriparatide or to any of its excipients. Hypersensitivity reactions have included angioedema and anaphylaxis [see Adverse Reactions (6.2)].

5 WARNINGS AND PRECAUTIONS

5.1 Osteosarcoma

An increase in the incidence of osteosarcoma (a malignant bone tumor) was observed in male and female rats treated with teriparatide. Osteosarcoma has been reported in patients treated with teriparatide in the post marketing setting; however, an increased risk of osteosarcoma has not been observed in observational studies in humans. There are limited data assessing the risk of osteosarcoma beyond 2 years of teriparatide use [see Dosage and Administration (2.3), Adverse Reactions (6.2), Nonclinical Toxicology (13.1)].

Avoid BONSITY use in patients with (these patients are at increased baseline risk of osteosarcoma):

- Open epiphyses (pediatric and young adult patients) (BONSITY is not approved in pediatric patients) [see Use in Specific Populations (8.4)].
- Metabolic bone diseases other than osteoporosis, including Paget's disease of the bone.
- Bone metastases or a history of skeletal malignancies.
- Prior external beam or implant radiation therapy involving the skeleton.
- Hereditary disorders predisposing to osteosarcoma.

5.2 Hypercalcemia and Cutaneous Calcification

Hypercalcemia

Teriparatide has not been studied in patients with pre-existing hypercalcemia. Teriparatide may cause hypercalcemia and may exacerbate hypercalcemia in patients with pre-existing hypercalcemia [see Adverse Reactions (6.1, 6.2)]. Avoid BONSITY in patients known to have an underlying hypercalcemic disorder, such as primary hyperparathyroidism.

Risk of Cutaneous Calcification Including Calciphylaxis

Serious reports of calciphylaxis and worsening of previously stable cutaneous calcification have been reported in the post-marketing setting in patients taking teriparatide. Risk factors for development of calciphylaxis include underlying autoimmune disease, kidney failure, and concomitant warfarin or systemic corticosteroid use. Discontinue BONSITY in patients who develop calciphylaxis or worsening of previously stable cutaneous calcification.

5.3 Risk of Urolithiasis

In clinical trials, the frequency of urolithiasis was similar in patients treated with teriparatide and patients treated with placebo. However, teriparatide has not been studied in patients with active urolithiasis. If BONSITY-treated patients have pre-existing hypercalciuria or suspected/known active urolithiasis, consider measuring urinary calcium excretion. Consider the risks and benefits of use in patients with active or recent urolithiasis because of the potential to exacerbate this condition.

5.4 Orthostatic Hypotension

BONSITY should be administered initially under circumstances in which the patient can sit or lie down if symptoms of orthostatic hypotension occur. In short-term clinical pharmacology studies of teriparatide in healthy volunteers, transient episodes of symptomatic orthostatic hypotension were observed in 5% of volunteers. Typically, these events began within 4 hours of dosing and resolved (without treatment) within a few minutes to a few hours. When transient orthostatic hypotension occurred, it happened within the first several doses, it was relieved by placing the person in a reclining position, and it did not preclude continued treatment.

5.5 Risk of Digoxin Toxicity

Hypercalcemia may predispose patients to digitalis toxicity because teriparatide transiently increases serum calcium. Consider the potential onset of signs and symptoms of digitalis toxicity when BONSITY is used in patients receiving digoxin [see Drug Interactions (7.1), Clinical Pharmacology (12.3)].

6 ADVERSE REACTIONS

6.1 Clinical Trials Experience

Because clinical studies are conducted under widely varying conditions, adverse reaction rates observed in the clinical studies of a drug cannot be directly compared to rates in the clinical studies of another drug and may not reflect the rates observed in practice.

Men with Primary or Hypogonadal Osteoporosis and Postmenopausal Women with Osteoporosis

The safety of teriparatide in the treatment of osteoporosis in men and postmenopausal women was assessed in two randomized, double-blind, placebo-controlled trials of 1382 patients (21% men, 79% women) aged 28 to 86 years (mean 67 years) [see Clinical Studies (14.1, 14.2)]. The median durations of the trials were 11 months for men and 19 months for women, with 691 patients exposed to teriparatide and 691 patients to placebo. All patients received 1000 mg of calcium plus at least 400 IU of vitamin D supplementation per day.

The incidence of all-cause mortality was 1% in the teriparatide group and 1% in the placebo group. The incidence of serious adverse events was 16% in the teriparatide group and 19% in the placebo group. Early discontinuation due to adverse events occurred in 7% in the teriparatide group and 6% in the placebo group.

Table 1 lists adverse events from these two trials that occurred in ≥2% of teriparatide-treated and more frequently than placebo-treated patients.

Table 1. Percentage of Patients with Adverse Events Reported by at Least 2% of Teriparatide-Treated Patients and in More Teriparatide-Treated Patients than Placebo-Treated Patients from the Two Principal Osteoporosis Trials in Women and Men (Adverse Events are Shown Without Attribution of Causality)
 | Teriparatide N=691 | Placebo N=691
Event Classification | (%) | (%)
Body as a Whole
Pain | 21.3 | 20.5
Headache | 7.5 | 7.4
Asthenia | 8.7 | 6.8
Neck pain | 3.0 | 2.7
Cardiovascular
Hypertension | 7.1 | 6.8
Angina pectoris | 2.5 | 1.6
Syncope | 2.6 | 1.4
Digestive System
Nausea | 8.5 | 6.7
Constipation | 5.4 | 4.5
Diarrhea | 5.1 | 4.6
Dyspepsia | 5.2 | 4.1
Vomiting | 3.0 | 2.3
Gastrointestinal disorder | 2.3 | 2.0
Tooth disorder | 2.0 | 1.3
Musculoskeletal
Arthralgia | 10.1 | 8.4
Leg cramps | 2.6 | 1.3
Nervous System
Dizziness | 8.0 | 5.4
Depression | 4.1 | 2.7
Insomnia | 4.3 | 3.6
Vertigo | 3.8 | 2.7
Respiratory System
Rhinitis | 9.6 | 8.8
Cough increased | 6.4 | 5.5
Pharyngitis | 5.5 | 4.8
Dyspnea | 3.6 | 2.6
Pneumonia | 3.9 | 3.3
Skin and Appendages
Rash | 4.9 | 4.5
Sweating | 2.2 | 1.7

Laboratory Findings

Serum Calcium - Teriparatide transiently increased serum calcium, with the maximal effect observed at approximately 4 to 6 hours post-dose. Serum calcium measured at least 16 hours post-dose was not different from pretreatment levels. In clinical trials, the frequency of at least 1 episode of transient hypercalcemia in the 4 to 6 hours after teriparatide administration was 11% of women and 6% of men treated with teriparatide compared to 2% of women and 0% of the men treated with placebo. The percentage of patients treated with teriparatide whose transient hypercalcemia was verified on consecutive measurements was 3% of women and 1% of men.

Urinary Calcium - Teriparatide increased urinary calcium excretion, but the frequency of hypercalciuria in clinical trials was similar for patients treated with teriparatide and placebo [see Clinical Pharmacology (12.2)].

Serum Uric Acid - Teriparatide increased serum uric acid concentrations. In clinical trials, 3% of teriparatide-treated patients had serum uric acid concentrations above the upper limit of normal compared with 1% of placebo-treated patients. However, the hyperuricemia did not result in an increase in gout, arthralgia, or urolithiasis.

Renal Function - No clinically important adverse renal effects were observed in clinical studies. Assessments included creatinine clearance; measurements of blood urea nitrogen (BUN), creatinine, and electrolytes in serum; urine specific gravity and pH; and examination of urine sediment.

Men and Women with Glucocorticoid-Induced Osteoporosis

The safety of teriparatide in the treatment of men and women with glucocorticoid-induced osteoporosis was assessed in a randomized, double-blind, active-controlled trial of 428 patients (19% men, 81% women) aged 22 to 89 years (mean 57 years) treated with ≥5 mg per day prednisone or equivalent for a minimum of 3 months [see Clinical Studies (14.3)]. The duration of the trial was 18 months with 214 patients exposed to teriparatide and 214 patients exposed to an oral daily bisphosphonate (active control). All patients received 1000 mg of calcium plus 800 IU of vitamin D supplementation per day.

There was no increase in mortality in the teriparatide group compared to the active control group. The incidence of serious adverse events was 21% in teriparatide patients and 18% in active control patients, and included pneumonia (3% teriparatide, 1% active control). Early discontinuation because of adverse events occurred in 15% of teriparatide patients and 12% of active control patients, and included dizziness (2% teriparatide, 0% active control).

Adverse events reported at a higher incidence in the teriparatide group and with at least a 2% difference in teriparatide-treated patients compared with active control-treated patients were: nausea (14%, 7%), gastritis (7%, 3%), pneumonia (6%, 3%), dyspnea (6%, 3%), insomnia (5%, 1%), anxiety (4%, 1%), and herpes zoster (3%, 1%), respectively.

6.2 Postmarketing Experience

Adverse Reactions from Postmarketing Spontaneous Reports

The following adverse reactions have been identified during post-approval use of teriparatide. Because these reactions are reported voluntarily from a population of uncertain size, it is not always possible to reliably estimate their frequency or establish a causal relationship to drug exposure.

- Cases of bone tumor and osteosarcoma have been reported rarely in the postmarketing period [see Warnings and Precautions (5.1)].
- Hypercalcemia greater than 13 mg/dL has been reported with teriparatide use.

Adverse events reported since market introduction that were temporally related to teriparatide therapy include the following:

- Allergic Reactions: Anaphylactic reactions, drug hypersensitivity, angioedema, urticaria
- Investigations: Hyperuricemia
- Respiratory System: Acute dyspnea, chest pain
- Musculoskeletal: Muscle spasms of the leg or back
- Other: Injection site reactions including injection site pain, swelling and bruising; oro-facial edema

Adverse Reactions from Observational Studies to Assess Incidence of Osteosarcoma

Two osteosarcoma surveillance safety studies (U.S. claims-based database studies) were designed to obtain data on the incidence rate of osteosarcoma among teriparatide-treated patients. In these two studies, three and zero osteosarcoma cases were identified among 379,283 and 153,316 teriparatide users, respectively. The study results suggest a similar risk for osteosarcoma between teriparatide users and their comparators. However, the interpretation of the study results calls for caution owing to the limitations of the data sources which do not allow for complete measurement and control for confounders.

7 DRUG INTERACTIONS

7.1 Digoxin

Sporadic case reports have suggested that hypercalcemia may predispose patients to digitalis toxicity. Teriparatide may transiently increase serum calcium. Consider the potential onset of signs and symptoms of digitalis toxicity when BONSITY is used in patients receiving digoxin [see Warnings and Precautions (5.5), Clinical Pharmacology (12.3)].

8 USE IN SPECIFIC POPULATIONS

8.1 Pregnancy

Risk Summary

There are no available data on BONSITY use in pregnant women to evaluate for drug-associated risk of major birth defects, miscarriage, or adverse maternal or fetal outcomes. Consider discontinuing BONSITY when pregnancy is recognized.

In animal reproduction studies, teriparatide increased skeletal deviations and variations in mouse offspring at subcutaneous doses equivalent to more than 60 times the recommended 20 mcg human daily dose (based on body surface area, mcg/m^2), and produced mild growth retardation and reduced motor activity in rat offspring at subcutaneous doses equivalent to more than 120 times the human dose (see Data).

The background risk of major birth defects and miscarriage for the indicated population is unknown. The background risk in the US general population of major birth defects is 2% to 4% and of miscarriage is 15% to 20% of clinically recognized pregnancies.

Data

Animal Data

In animal reproduction studies, pregnant mice received teriparatide during organogenesis at subcutaneous doses equivalent to 8 to 267 times the human dose (based on body surface area, mcg/m^2). At subcutaneous doses ≥60 times the human dose, the fetuses showed an increased incidence of skeletal deviations or variations (interrupted rib, extra vertebra or rib). When pregnant rats received teriparatide during organogenesis at subcutaneous doses 16 to 540 times the human dose, the fetuses showed no abnormal findings.

In a perinatal/postnatal study in pregnant rats dosed subcutaneously from organogenesis through lactation, mild growth retardation was observed in female offspring at doses ≥120 times the human dose. Mild growth retardation in male offspring and reduced motor activity in both male and female offspring were observed at maternal doses of 540 times the human dose. There were no developmental or reproductive effects in mice or rats at doses 8 or 16 times the human dose, respectively.

8.2 Lactation

Risk Summary

It is not known whether teriparatide is excreted in human milk, affects human milk production, or has effects on the breast fed infant. Avoid BONSITY use in women who are breastfeeding.

8.4 Pediatric Use

The safety and effectiveness of teriparatide have not been established in pediatric patients. Pediatric patients are at higher baseline risk of osteosarcoma because of open epiphyses [see Warnings and Precautions (5.1)].

8.5 Geriatric Use

Of the patients who received teriparatide in the osteoporosis trial of 1637 postmenopausal women, 75% were 65 years of age and older and 23% were 75 years of age and older. Of the patients who received teriparatide in the trial of 437 men with primary or hypogonadal osteoporosis, 39% were 65 years of age and over and 13% were 75 years of age and over. Of the 214 patients who received teriparatide in the glucocorticoid induced osteoporosis trial, 28% were 65 years of age and older and 9% were 75 years of age and older. No overall differences in safety or effectiveness of teriparatide have been observed between patients 65 years of age and older and younger adult patients.

8.6 Hepatic Impairment

No studies have been performed in patients with hepatic impairment [see Clinical Pharmacology (12.3)].

8.7 Renal Impairment

In 5 patients with severe renal impairment (CrCl <30 mL/minute), the AUC and T1/2 of teriparatide were increased by 73% and 77%, respectively. Maximum serum concentration of teriparatide was not increased. It is unknown whether teriparatide alters the underlying metabolic bone disease seen in chronic renal impairment [see Clinical Pharmacology (12.3)].

10 OVERDOSAGE

In postmarketing spontaneous reports, there have been cases of medication errors in which the entire contents (up to 800 mcg) (40 times the recommended dose) of the teriparatide prefilled delivery device (pen) have been administered as a single dose. Transient events reported have included nausea, weakness/lethargy and hypotension. No fatalities associated with overdose have been reported. Additional signs, symptoms, and complications of teriparatide overdosage may include a delayed hypercalcemic effect, vomiting, dizziness, and headache.

Overdose Management - There is no specific antidote for a teriparatide overdosage. Treatment of suspected overdosage should include discontinuation of BONSITY, monitoring of serum calcium and phosphorus, and implementation of appropriate supportive measures, such as hydration.

11 DESCRIPTION

BONSITY (teriparatide injection) is a recombinant human parathyroid hormone analog (PTH 1-34). It has an identical sequence to the 34 N-terminal amino acids (the biologically active region) of the 84-amino acid human parathyroid hormone.

The molecular formula of teriparatide is C181H291N55O51S2 and the molecular weight is 4117.8 daltons. Its amino acid sequence is shown below:

Teriparatide is manufactured using a strain of Pseudomonas fluorescens modified by recombinant DNA technology. BONSITY is supplied as a sterile, colorless, clear, isotonic solution in a glass cartridge which is pre-assembled into a single-patient-use delivery device (pen) for subcutaneous injection. Each pen is filled with volume to allow delivery of 2.24 mL. Each mL contains 250 mcg teriparatide (as a free base), 0.41 mg glacial acetic acid, 0.10 mg sodium acetate, 45.4 mg mannitol, 3 mg metacresol, and water for injection. The drug product is a pH 4.0 solution.

Each cartridge, pre-assembled into a delivery device, delivers 20 mcg of teriparatide per dose each day for up to 28 days. Each device contains additional volume to allow troubleshooting of the device 2 times.

12 CLINICAL PHARMACOLOGY

12.1 Mechanism of Action

Endogenous 84-amino acid parathyroid hormone (PTH) is the primary regulator of calcium and phosphate metabolism in bone and kidney. Physiological actions of PTH include regulation of bone metabolism, renal tubular reabsorption of calcium and phosphate, and intestinal calcium absorption. The biological actions of PTH and teriparatide are mediated through binding to specific high-affinity cell-surface receptors. Teriparatide and the 34 N-terminal amino acids of PTH bind to these receptors with the same affinity and have the same physiological actions on bone and kidney. Teriparatide is not expected to accumulate in bone or other tissues.

The skeletal effects of teriparatide depend upon the pattern of systemic exposure. Once-daily administration of teriparatide stimulates new bone formation on trabecular and cortical (periosteal and/or endosteal) bone surfaces by preferential stimulation of osteoblastic activity over osteoclastic activity. In monkey studies, teriparatide improved trabecular microarchitecture and increased bone mass and strength by stimulating new bone formation in both cancellous and cortical bone. In humans, the anabolic effects of teriparatide manifest as an increase in skeletal mass, an increase in markers of bone formation and resorption, and an increase in bone strength. By contrast, continuous excess of endogenous PTH, as occurs in hyperparathyroidism, may be detrimental to the skeleton because bone resorption may be stimulated more than bone formation.

12.2 Pharmacodynamics

Pharmacodynamics in Men with Primary or Hypogonadal Osteoporosis and Postmenopausal Women with Osteoporosis

Effects on Mineral Metabolism - Teriparatide affects calcium and phosphorus metabolism in a pattern consistent with the known actions of endogenous PTH (e.g., increases serum calcium and decreases serum phosphorus).

Serum Calcium Concentrations - When teriparatide 20 mcg was administered once daily, the serum calcium concentration increased transiently, beginning approximately 2 hours after dosing and reaching a maximum concentration between 4 and 6 hours (median increase, 0.4 mg/dL). The serum calcium concentration began to decline approximately 6 hours after dosing and returned to baseline by 16 to 24 hours after each dose.

In a clinical study of postmenopausal women with osteoporosis, the median peak serum calcium concentration measured 4 to 6 hours after dosing with teriparatide (20 mcg subcutaneous once daily) was 9.68 mg/dL at 12 months. The peak serum calcium remained below 11 mg/dL in >99% of women at each visit. Sustained hypercalcemia was not observed.

In this study, 11.1% of women treated with teriparatide had at least 1 serum calcium value above the upper limit of normal (ULN) (10.6 mg/dL) compared with 1.5% of women treated with placebo. The percentage of women treated with teriparatide whose serum calcium was above the ULN on consecutive 4- to 6-hour post-dose measurements was 3% compared with 0.2% of women treated with placebo. In these women, calcium supplements and/or teriparatide doses were reduced. The timing of these dose reductions was at the discretion of the investigator. Teriparatide dose adjustments were made at varying intervals after the first observation of increased serum calcium (median 21 weeks). During these intervals, there was no evidence of progressive increases in serum calcium.

In a clinical study of men with either primary or hypogonadal osteoporosis, the effects on serum calcium were similar to those observed in postmenopausal women. The median peak serum calcium concentration measured 4 to 6 hours after dosing with teriparatide was 9.44 mg/dL at 12 months. The peak serum calcium remained below 11 mg/dL in 98% of men at each visit. Sustained hypercalcemia was not observed.

In this study, 6% of men treated with teriparatide daily had at least 1 serum calcium value above the ULN (10.6 mg/dL) compared with none of the men treated with placebo. The percentage of men treated with teriparatide whose serum calcium was above the ULN on consecutive measurements was 1.3% (2 men) compared with none of the men treated with placebo. Calcium supplementation was reduced in these men [see Warnings and Precautions (5.2), Adverse Reactions (6.1)].

In a clinical study of women previously treated for 18 to 39 months with raloxifene (n=26) or alendronate (n=33), mean serum calcium >12 hours after teriparatide treatment was increased by 0.36 to 0.56 mg/dL, after 1 to 6 months of teriparatide treatment compared with baseline. Of the women pretreated with raloxifene, 3 (11.5%) had a serum calcium >11 mg/dL, and of those pretreated with alendronate, 3 (9.1%) had a serum calcium >11 mg/dL. The highest serum calcium reported was 12.5 mg/dL. None of the women had symptoms of hypercalcemia. There were no placebo controls in this study.

In the study of patients with glucocorticoid-induced osteoporosis, the effects of teriparatide on serum calcium were similar to those observed in postmenopausal women with osteoporosis not taking glucocorticoids.

Urinary Calcium Excretion - In a clinical study of postmenopausal women with osteoporosis who received 1000 mg of supplemental calcium and at least 400 IU of vitamin D, daily teriparatide increased urinary calcium excretion. The median urinary excretion of calcium was 190 mg/day at 6 months and 170 mg/day at 12 months. These levels were 30 mg/day and 12 mg/day higher, respectively, than in women treated with placebo. The incidence of hypercalciuria (>300 mg/day) was similar in the women treated with teriparatide or placebo.

In a clinical study of men with either primary or hypogonadal osteoporosis who received 1000 mg of supplemental calcium and at least 400 IU of vitamin D, daily teriparatide had inconsistent effects on urinary calcium excretion. The median urinary excretion of calcium was 220 mg/day at 1 month and 210 mg/day at 6 months. These levels were 20 mg/day higher and 8 mg/day lower, respectively, than in men treated with placebo. The incidence of hypercalciuria (>300 mg/day) was similar in the men treated with teriparatide or placebo.

Phosphorus and Vitamin D - In single-dose studies, teriparatide produced transient phosphaturia and mild transient reductions in serum phosphorus concentration. However, hypophosphatemia (<2.4 mg/dL) was not observed in clinical trials with teriparatide.

In clinical trials of daily teriparatide, the median serum concentration of 1,25-dihydroxyvitamin D was increased at 12 months by 19% in women and 14% in men, compared with baseline. In the placebo group, this concentration decreased by 2% in women and increased by 5% in men. The median serum 25-hydroxyvitamin D concentration at 12 months was decreased by 19% in women and 10% in men compared with baseline. In the placebo group, this concentration was unchanged in women and increased by 1% in men.

In the study of patients with glucocorticoid-induced osteoporosis, the effects of teriparatide on serum phosphorus were similar to those observed in postmenopausal women with osteoporosis not taking glucocorticoids.

Effects on Markers of Bone Turnover - Daily administration of teriparatide to men and postmenopausal women with osteoporosis in clinical studies stimulated bone formation, as shown by increases in the formation markers serum bone-specific alkaline phosphatase (BSAP) and procollagen I carboxy-terminal propeptide (PICP). Data on biochemical markers of bone turnover were available for the first 12 months of treatment. Peak concentrations of PICP at 1 month of treatment were approximately 41% above baseline, followed by a decline to near-baseline values by 12 months. BSAP concentrations increased by 1 month of treatment and continued to rise more slowly from 6 through 12 months. The maximum increases of BSAP were 45% above baseline in women and 23% in men. After discontinuation of therapy, BSAP concentrations returned toward baseline. The increases in formation markers were accompanied by secondary increases in the markers of bone resorption: urinary N-telopeptide (NTX) and urinary deoxypyridinoline (DPD), consistent with the physiological coupling of bone formation and resorption in skeletal remodeling. Changes in BSAP, NTX, and DPD were lower in men than in women, possibly because of lower systemic exposure to teriparatide in men.

In the study of patients with glucocorticoid-induced osteoporosis, the effects of teriparatide on serum markers of bone turnover were similar to those observed in postmenopausal women with osteoporosis not taking glucocorticoids.

12.3 Pharmacokinetics

The pharmacokinetic parameters of teriparatide following single subcutaneous administration of BONSITY in patients with osteoporosis are shown in Table 2.

Table 2. Pharmacokinetic Parameters of Teriparatide Following Administration of a Single Dose, 20 mcg, of BONSITY
 | Mean ± S.D. | n
Tmax (hour) [Tmax = median (minimum, maximum)] | 0.25 (0.12, 1.08) | 83
Cmax (pg/mL) | 109.5 ± 62.8 | 83
AUC0-t (pg∙hr/mL) | 134.8 ± 79.7 | 83
AUC0-inf (pg∙hr/mL) | 149.8 ± 68.1 | 72
t1/2 (hour) | 0.79 ± 0.35 | 72
Arithmetic mean ± S.D.;

Absorption — Teriparatide is absorbed after subcutaneous injection; the absolute bioavailability is approximately 95% based on pooled data from 20-, 40-, and 80-mcg doses (1-, 2-, and 4-times the recommended dosage, respectively). The peptide reaches peak serum concentrations about 30 minutes after subcutaneous injection of a 20-mcg dose and declines to non-quantifiable concentrations within 3 hours.

Distribution — Volume of distribution following intravenous injection is approximately 0.12 L/kg.

Elimination — Systemic clearance of teriparatide (approximately 62 L/hour in women and 94 L/hour in men) exceeds the rate of normal liver plasma flow, consistent with both hepatic and extra-hepatic clearance.

No metabolism or excretion studies have been performed with teriparatide. Peripheral metabolism of PTH is believed to occur by non-specific enzymatic mechanisms in the liver followed by excretion via the kidneys.

Specific Populations

Geriatric Patients - No age-related differences in teriparatide pharmacokinetics were detected (range 31 to 85 years).

Male and Female Patients - Although systemic exposure to teriparatide was approximately 20% to 30% lower in men than women, the recommended dosage for men and women is the same.

Racial Groups - The influence of race has not been determined.

Patients with Renal Impairment - No pharmacokinetic differences were identified in 11 patients with creatinine clearance (CrCl) 30 to 72 mL/minute administered a single dose of teriparatide. In 5 patients with severe renal impairment (CrCl <30 mL/minute), the AUC and T1/2 of teriparatide were increased by 73% and 77%, respectively. Maximum serum concentration of teriparatide was not increased. No studies have been performed in patients undergoing dialysis for chronic renal failure.

Patients with Hepatic Impairment - No studies have been performed in patients with hepatic impairment. Non-specific proteolytic enzymes in the liver (possibly Kupffer cells) cleave PTH(1-34) and PTH(1-84) into fragments that are cleared from the circulation mainly by the kidney.

Drug Interaction Studies

Digoxin — In a study of 15 healthy people administered digoxin daily to steady state, a single teriparatide dose did not alter the effect of digoxin on the systolic time interval (from electrocardiographic Q-wave onset to aortic valve closure, a measure of digoxin's calcium-mediated cardiac effect).

Hydrochlorothiazide — In a study of 20 healthy people, the coadministration of hydrochlorothiazide 25 mg with 40 mcg of teriparatide (2 times the recommended dose) did not affect the serum calcium response to teriparatide. The 24-hour urine excretion of calcium was reduced by a clinically unimportant amount (15%). The effect of coadministration of a higher dose of hydrochlorothiazide with teriparatide on serum calcium levels has not been studied.

Furosemide — In a study of 9 healthy people and 17 patients with CrCl 13 to 72 mL/minute, coadministration of intravenous furosemide (20 to 100 mg) with teriparatide 40 mcg (2 times the recommended dose) resulted in small increases in the serum calcium (2%) and 24 hour urine calcium (37%); however, these changes did not appear to be clinically important.

12.6 Immunogenicity

The observed incidence of anti-drug antibodies is highly dependent on the sensitivity and specificity of the assay. Differences in assay methods preclude meaningful comparisons of the incidence of anti-drug antibodies in the studies described below with the incidence of anti-drug antibodies in other studies, including those of teriparatide or of other teriparatide products.

The immunogenicity profile of BONSITY was evaluated in a 24-week randomized trial comparing the effects of BONSITY 20 mcg daily with another teriparatide product 20 mcg daily. In this trial, 2.2% (2/90) subjects who received BONSITY and 2.2% (2/91) subjects who received the other teriparatide product had detectable antibodies to teriparatide and one out of the two BONSITY treated patients developed neutralizing antibodies to teriparatide.

13 NONCLINICAL TOXICOLOGY

13.1 Carcinogenesis, Mutagenesis, Impairment of Fertility

Carcinogenesis

Two carcinogenicity bioassays were conducted in Fischer 344 rats. In the first study, male and female rats were given daily subcutaneous teriparatide injections of 5, 30, or 75 mcg/kg/day for 24 months from 2 months of age. These doses resulted in rat systemic exposures that were 3, 20, and 60 times higher than the systemic exposure observed in humans, respectively, following a subcutaneous dose of 20 mcg (based on AUC comparison). Teriparatide treatment resulted in a marked dose-related increase in the incidence of osteosarcoma, a rare malignant bone tumor, in both male and female rats. Osteosarcomas were observed at all doses and the incidence reached 40% to 50% in the high-dose groups. Teriparatide also caused a dose-related increase in osteoblastoma and osteoma in both sexes. No osteosarcomas, osteoblastomas or osteomas were observed in untreated control rats. The bone tumors in rats occurred in association with a large increase in bone mass and focal osteoblast hyperplasia.

The second 2-year study was carried out in order to determine the effect of treatment duration and animal age on the development of bone tumors. Female rats were treated for different periods between 2 and 26 months of age with subcutaneous doses of 5 and 30 mcg/kg (equivalent to 3 and 20 times the human exposure at the 20-mcg dose, respectively, based on AUC comparison). The study showed that the occurrence of osteosarcoma, osteoblastoma and osteoma was dependent upon dose and duration of exposure. Bone tumors were observed when immature 2-month old rats were treated with 30 mcg/kg/day of teriparatide for 24 months or with 5 or 30 mcg/kg/day of teriparatide for 6 months. Bone tumors were also observed when mature 6-month old rats were treated with 30 mcg/kg/day of teriparatide for 6 or 20 months. Tumors were not detected when mature 6-month old rats were treated with 5 mcg/kg/day of teriparatide for 6 or 20 months. The results did not demonstrate a difference in susceptibility to bone tumor formation, associated with teriparatide treatment, between mature and immature rats.

No bone tumors were detected in a long-term monkey study [see Nonclinical Toxicology (13.2)].

Mutagenesis

Teriparatide was not genotoxic in any of the following test systems: the Ames test for bacterial mutagenesis; the mouse lymphoma assay for mammalian cell mutation; the chromosomal aberration assay in Chinese hamster ovary cells, with and without metabolic activation; and the in vivo micronucleus test in mice.

Impairment of Fertility

No effects on fertility were observed in male and female rats given subcutaneous teriparatide doses of 30, 100, or 300 mcg/kg/day prior to mating and in females continuing through gestation Day 6 (16 to 160 times the human dose of 20 mcg based on surface area, mcg/m^2).

13.2 Animal Toxicology and/or Pharmacology

In single-dose rodent studies using subcutaneous injection of teriparatide, no mortality was seen in rats given doses of 1000 mcg/kg (540 times the human dose based on surface area, mcg/m^2) or in mice given 10,000 mcg/kg (2700 times the human dose based on surface area, mcg/m^2).

In a long-term study, skeletally mature ovariectomized female monkeys (N=30 per treatment group) were given either daily subcutaneous teriparatide injections of 5 mcg/kg or vehicle. Following the 18-month treatment period, the monkeys were removed from teriparatide treatment and were observed for an additional 3 years. The 5 mcg/kg dose resulted in systemic exposures that were approximately 6 times higher than the systemic exposure observed in humans following a subcutaneous dose of 20 mcg (based on AUC comparison). Bone tumors were not detected by radiographic or histologic evaluation in any monkey in the study.

14 CLINICAL STUDIES

14.1 Treatment of Osteoporosis in Postmenopausal Women

The safety and efficacy of once-daily teriparatide, median exposure of 19 months, were examined in a double-blind, multicenter, placebo-controlled clinical study of 1637 postmenopausal women with osteoporosis. In this study 541 postmenopausal women were treated with 20 mcg teriparatide subcutaneously once daily.

All women received 1000 mg of calcium and at least 400 IU of vitamin D per day. Baseline and endpoint spinal radiographs were evaluated using the semiquantitative scoring. Ninety percent of the women in the study had 1 or more radiographically diagnosed vertebral fractures at baseline. The primary efficacy endpoint was the occurrence of new radiographically diagnosed vertebral fractures defined as changes in the height of previously undeformed vertebrae. Such fractures are not necessarily symptomatic.

Effect on Fracture Incidence

New Vertebral Fractures — Teriparatide, when taken with calcium and vitamin D and compared with calcium and vitamin D alone, reduced the risk of 1 or more new vertebral fractures from 14.3% of women in the placebo group to 5.0% in the teriparatide group (444 of the 541 patients treated with 20 mcg once daily of teriparatide were included in this analysis). This difference was statistically significant (p <0.001); the absolute reduction in risk was 9.3% and the relative reduction was 65%. Teriparatide was effective in reducing the risk for vertebral fractures regardless of age, baseline rate of bone turnover, or baseline BMD (see Table 3).

Table 3. Effect of Teriparatide on Risk of Vertebral Fractures in Postmenopausal Women with Osteoporosis
Percent of Women With Fracture
 | Teriparatide (N=444) | Placebo (N=448) | Absolute Risk Reduction (%, 95% CI) | Relative Risk Reduction (%, 95% CI)
New fracture (≥1) | 5.0 [p ≤0.001 compared with placebo.] | 14.3 | 9.3 (5.5-13.1) | 65 (45-78)
1 fracture | 3.8 | 9.4
2 fractures | 0.9 | 2.9
≥3 fractures | 0.2 | 2.0

New Nonvertebral Osteoporotic Fractures — Teriparatide significantly reduced the risk of any nonvertebral fracture from 5.5% in the placebo group to 2.6% in the teriparatide group (p <0.05). The absolute reduction in risk was 2.9% and the relative reduction was 53%. The incidence of new nonvertebral fractures in the teriparatide group compared with the placebo group was ankle/foot (0.2%, 0.7%), hip (0.2%, 0.7%), humerus (0.4%, 0.4%), pelvis (0%, 0.6%), ribs (0.6%, 0.9%), wrist (0.4%, 1.3%), and other sites (1.1%, 1.5%), respectively.

The cumulative percentage of postmenopausal women with osteoporosis who sustained new nonvertebral fractures was lower in women treated with teriparatide than in women treated with placebo (see Figure 1).

Figure 1: Cumulative Percentage of Postmenopausal Women with Osteoporosis Sustaining New Nonvertebral Osteoporotic Fractures

Effect on Bone Mineral Density (BMD)

Teriparatide increased lumbar spine BMD in postmenopausal women with osteoporosis. Statistically significant increases were seen at 3 months and continued throughout the treatment period. Postmenopausal women with osteoporosis who were treated with teriparatide had statistically significant increases in BMD from baseline to endpoint at the lumbar spine, femoral neck, total hip, and total body (see Table 4).

Table 4. Mean Percent Change in BMD from Baseline to Endpoint [Intent-to-treat analysis, last observation carried forward.] in Postmenopausal Women with Osteoporosis, Treated with Teriparatide or Placebo for a Median of 19 Months
 | Teriparatide N=541 | Placebo N=544
Lumbar spine BMD | 9.7 [p <0.001 compared with placebo.] | 1.1
Femoral neck BMD | 2.8 [p <0.05 compared with placebo.] | -0.7
Total hip BMD | 2.6‡ | -1.0
Trochanter BMD | 3.5‡ | -0.2
Intertrochanter BMD | 2.6‡ | -1.3
Ward's triangle BMD | 4.2‡ | -0.8
Total body BMD | 0.6‡ | -0.5
Distal 1/3 radius BMD | -2.1 | -1.3
Ultradistal radius BMD | -0.1 | -1.6

Teriparatide treatment increased lumbar spine BMD from baseline in 96% of postmenopausal women treated. Seventy-two percent of patients treated with teriparatide achieved at least a 5% increase in spine BMD, and 44% gained 10% or more.

Both treatment groups lost height during the trial. The mean decreases were 3.61 and 2.81 mm in the placebo and teriparatide groups, respectively.

Bone Histology

The effects of teriparatide on bone histology were evaluated in iliac crest biopsies of 35 postmenopausal women treated for 12 to 24 months with calcium and vitamin D and teriparatide. Normal mineralization was observed with no evidence of cellular toxicity. The new bone formed with teriparatide was of normal quality (as evidenced by the absence of woven bone and marrow fibrosis).

14.2 Treatment to Increase Bone Mass in Men with Primary or Hypogonadal Osteoporosis

The safety and efficacy of once-daily teriparatide, median exposure of 10 months, were examined in a double-blind, multicenter, placebo-controlled clinical study of 437 men with either primary (idiopathic) or hypogonadal osteoporosis. In this study, 151 men received 20 mcg of teriparatide given subcutaneously once daily. All men received 1000 mg of calcium and at least 400 IU of vitamin D per day. The primary efficacy endpoint was change in lumbar spine BMD.

Teriparatide increased lumbar spine BMD in men with primary or hypogonadal osteoporosis. Statistically significant increases were seen at 3 months and continued throughout the treatment period. Teriparatide was effective in increasing lumbar spine BMD regardless of age, baseline rate of bone turnover, and baseline BMD. The effects of teriparatide at additional skeletal sites are shown in Table 5.

Teriparatide treatment for a median of 10 months increased lumbar spine BMD from baseline in 94% of men treated. Fifty-three percent of patients treated with teriparatide achieved at least a 5% increase in spine BMD, and 14% gained 10% or more.

Table 5. Mean Percent Change in BMD from Baseline to Endpoint [Intent-to-treat analysis, last observation carried forward.] in Men with Primary or Hypogonadal Osteoporosis, Treated with Teriparatide or Placebo for a Median of 10 Months
 | Teriparatide N=151 | Placebo N=147
Lumbar spine BMD | 5.9 [p <0.001 compared with placebo.] | 0.5
Femoral neck BMD | 1.5 [p <0.05 compared with placebo.] | 0.3
Total hip BMD | 1.2 | 0.5
Trochanter BMD | 1.3 | 1.1
Intertrochanter BMD | 1.2 | 0.6
Ward's triangle BMD | 2.8 | 1.1
Total body BMD | 0.4 | -0.4
Distal 1/3 radius BMD | -0.5 | -0.2
Ultradistal radius BMD | -0.5 | -0.3

14.3 Treatment of Men and Women with Glucocorticoid-Induced Osteoporosis

The efficacy of teriparatide for treating glucocorticoid-induced osteoporosis was assessed in a randomized, double-blind, active-controlled trial of 428 patients (19% men, 81% women) aged 22 to 89 years (mean 57 years) treated with ≥5 mg/day prednisone or equivalent for a minimum of 3 months. The duration of the trial was 18 months. In the trial 214 patients were treated with teriparatide 20 mcg given subcutaneously once daily. In the teriparatide group, the baseline median glucocorticoid dose was 7.5 mg/day and the baseline median duration of glucocorticoid use was 1.5 years. The mean (SD) baseline lumbar spine BMD was 0.85 ± 0.13 g/cm^2 and lumbar spine BMD T-score was –2.5 ± 1 (number of standard deviations below the mean BMD value for healthy adults). A total of 30% of patients had prevalent vertebral fracture(s) and 43% had prior non-vertebral fracture(s). The patients had chronic rheumatologic, respiratory or other diseases that required sustained glucocorticoid therapy. All patients received 1000 mg of calcium plus 800 IU of vitamin D supplementation per day.

Because of differences in mechanism of action (anabolic vs. anti-resorptive) and lack of clarity regarding differences in BMD as an adequate predictor of fracture efficacy, data on the active comparator are not presented.

Effect on Bone Mineral Density (BMD)

In patients with glucocorticoid-induced osteoporosis, teriparatide increased lumbar spine BMD compared with baseline at 3 months through 18 months of treatment. In patients treated with teriparatide, the mean percent change in BMD from baseline to endpoint was 7.2% at the lumbar spine, 3.6% at the total hip, and 3.7% at the femoral neck (p<0.001 all sites). The relative treatment effects of teriparatide were consistent in subgroups defined by gender, age, geographic region, body mass index, underlying disease, prevalent vertebral fracture, baseline glucocorticoid dose, prior bisphosphonate use, and glucocorticoid discontinuation during trial.

16 HOW SUPPLIED/STORAGE AND HANDLING

16.1 How Supplied

BONSITY (teriparatide injection) is a colorless solution, available as single-patient-use prefilled pens in the following package size:

- 560 mcg/2.24 mL (250 mcg/mL) NDC 47781-852-89.

16.2 Storage and Handling

- The BONSITY delivery device should be stored under refrigeration at 2°C to 8°C (36°F to 46°F) at all times.
- Recap the delivery device when not in use to protect the cartridge from physical damage and light.
- When using BONSITY, minimize the time out of the refrigerator; deliver the dose immediately following removal from the refrigerator.
- Do not freeze. Do not use BONSITY if it has been frozen.
- Throw away the device 28 days after first use.

17 PATIENT COUNSELING INFORMATION

Advise the patient to read the FDA-approved patient labeling (Medication Guide and the User Manual) before starting BONSITY and each time the prescription is renewed. Failure to follow the instructions may result in inaccurate dosing.

Osteosarcoma

Patients should be made aware that in rats, teriparatide caused an increase in the incidence of osteosarcoma (a malignant bone tumor). Although cases of osteosarcoma have been reported in patients using teriparatide, no increased risk of osteosarcoma was observed in adult humans treated with teriparatide [see Warnings and Precautions (5.1)].

Hypercalcemia

Instruct patients taking BONSITY to contact a health care provider if they develop persistent symptoms of hypercalcemia (e.g., nausea, vomiting, constipation, lethargy, muscle weakness) [see Warnings and Precautions (5.2)].

Orthostatic Hypotension

When initiating BONSITY treatment, instruct patients to be prepared to immediately sit or lie down during or after administration in case they feel lightheaded or have palpitations after the injection. Instruct patients to sit or lie down until the symptoms resolve. If symptoms persist or worsen, instruct patients to consult a healthcare provider before continuing treatment [see Warnings and Precautions (5.4)].

Other Osteoporosis Treatment Modalities

Patients should be informed regarding the roles of supplemental calcium and/or vitamin D.

Use of Delivery Device (Pen)

Instruct patients and caregivers who administer BONSITY on how to properly use the delivery device (refer to User Manual), to properly dispose of needles, and not to share their delivery device with other patients. Instruct patients and caregivers who administer BONSITY that the contents of the delivery device should not be transferred to a syringe.

Inform patients that each BONSITY delivery device can be used for up to 28 days. Instruct patients to discard the BONSITY delivery device 28 days after first use, even if it still contains some unused solution. Instruct patients not to use BONSITY after the expiration date printed on the delivery device and packaging.

BONSITY® is a registered trademark of Pfenex, Inc.

Distributed by:
Alvogen, Inc.
Morristown, NJ 07960 USA

PI852-00

Medication Guide
BONSITY® (bon si tee)
teriparatide injection
for subcutaneous use

Read this Medication Guide before you start using BONSITY and each time you get a refill. There may be new information. Also, read the User Manual that comes with the BONSITY delivery device (pen) for information on how to use the device to inject your medicine the right way. This Medication Guide does not take the place of talking with your healthcare provider about your medical condition or your treatment.

What is the most important information I should know about BONSITY?
Possible bone cancer. During drug testing, the medicine in BONSITY caused some rats to develop a bone cancer called osteosarcoma. Studies in people have not shown that teriparatide increases your chance of getting osteosarcoma. There is little information about the chance of getting osteosarcoma in patients using teriparatide beyond 2 years.

What is BONSITY?
BONSITY is a prescription medicine used to:

- treat post-menopausal women who have osteoporosis who are at high risk for having broken bones (fractures) or who cannot use other osteoporosis treatments. BONSITY can lessen the chance of broken bones (fractures) in the spine and other bones in postmenopausal women with osteoporosis.
- increase the bone mass in men with primary or hypogonadal osteoporosis who are at high risk for having broken bones (fractures) or who cannot use other osteoporosis treatments.
- treat both men and women with osteoporosis due to use of glucocorticoid medicines, such as prednisone, for several months, who are at high risk for having broken bones (fractures) or who cannot use other osteoporosis treatments.

It is not known if BONSITY is safe and effective in children.
BONSITY should not be used in children and young adults whose bones are still growing.

Who should not use BONSITY?
Do not use BONSITY if you:

- are allergic to any of the ingredients in BONSITY. See the end of this Medication Guide for a complete list of the ingredients in BONSITY.

Symptoms of a serious allergic reaction of BONSITY may include swelling of the face, lips, tongue or throat that may cause difficulty in breathing or swallowing. Call your healthcare provider right away or get emergency medical help if you get any of these symptoms.

What should I tell my healthcare provider before using BONSITY?
Before you use BONSITY, tell your healthcare provider about all of your medical conditions, including if you:

- have a certain bone disease called Paget's disease or other bone disease.
- have bone cancer or have had a history of bone cancer.
- are a young adult whose bones are still growing.
- have had radiation therapy.
- are affected with a condition that runs in your family that can increase your chance of getting cancer in your bones.
- have or have had too much calcium in your blood (hypercalcemia).
- have or have had a skin condition with painful sores or wounds caused by too much calcium.
- have or have had kidney stones.
- take medicines that contain digoxin.
- are pregnant or plan to become pregnant. It is not known if BONSITY will harm your unborn baby.
- are breast-feeding or plan to breast feed. It is not known if BONSITY passes into your breastmilk. You should not breast-feed while taking BONSITY.

Tell your healthcare provider about all the medicines you take, including prescription and over-the-counter medicines, vitamins, and herbal supplements.
Know the medicines you take. Keep a list of them to show your healthcare provider and pharmacist when you get a new medicine.

How should I use BONSITY?

- Read the detailed Instructions for Use (User Manual) included with your BONSITY delivery device.
- Use BONSITY exactly as your healthcare provider tells you to. Your healthcare provider will tell you how much BONSITY to use and when to use it.
- Before you try to inject BONSITY yourself, a healthcare provider should teach you how to use the BONSITY delivery device to give your injection the right way.
- Inject BONSITY 1 time each day in your thigh or abdomen (lower stomach area). Do not inject into a vein or a muscle. Talk to a healthcare provider about how to rotate injection sites.
- The BONSITY delivery device has enough medicine for 28 days. It is set to give a 20-microgram dose of medicine each day. Do not inject all the medicine in the BONSITY delivery device at any one time.
- Do not transfer the medicine from the BONSITY delivery device to a syringe. This can result in taking the wrong dose of BONSITY. If you do not have pen needles to use with your BONSITY delivery device, talk with your healthcare provider.
- BONSITY should look clear and colorless. Do not use BONSITY if it has particles in it, or if it is cloudy or colored.
- Inject BONSITY right away after you take the delivery device out of the refrigerator.
- After each use, safely remove the needle, recap the delivery device, and put it back in the refrigerator right away.
- When you inject the first few doses of BONSITY, make sure you are in a place where you can sit or lie down right away in case you feel dizzy or have an abnormal heartbeat after the injection.
- Do not take more than 1 injection in the same day.
- Do not share your BONSITY delivery device with other people.
- If you take more BONSITY than prescribed, call your healthcare provider. If you take too much BONSITY, you may have nausea, vomiting, weakness, or dizziness.
- You should not use BONSITY for more than 2 years over your lifetime unless your healthcare provider finds that you need longer treatment because you have a high chance of breaking your bones.

If your healthcare provider recommends calcium and vitamin D supplements, you can take them at the same time you take BONSITY.

What are the possible side effects of BONSITY?
BONSITY may cause serious side effects, including:

- See "What is the most important information I should know about BONSITY?"
- Bone cancer (osteosarcoma): Tell your healthcare provider right away if you have pain in your bones, pain in any areas of your body that does not go away, or any new or unusual lumps or swelling under your skin that is tender to touch.
- Increased calcium in your blood. Tell your healthcare provider if you have nausea, vomiting, constipation, low energy, or muscle weakness. These may be signs there is too much calcium in your blood.
- Worsening of your kidney stones. If you have or have had kidney stones your healthcare provider may check the calcium levels in your urine while you use BONSITY to see if there is worsening of this condition.
- Decrease in blood pressure when you change positions. Some people may feel dizzy, get a fast heartbeat, or feel light-headed right after the first few doses of BONSITY. This usually happens within 4 hours of taking BONSITY and goes away within a few hours. For the first few doses, give your injections of BONSITY in a place where you can sit or lie down right away if you get these symptoms. If your symptoms get worse or do not go away, contact your healthcare provider before you continue using BONSITY.

The most common side effects of BONSITY include:

- pain
- nausea
- joint aches

These are not all the possible side effects of BONSITY. For more information, ask your healthcare provider or pharmacist.
Call your doctor for medical advice about side effects. You may report side effects to FDA at 1-800-FDA-1088.

How should I store BONSITY?

- Store BONSITY in the refrigerator between 36°F to 46°F (2°C to 8°C) until ready to use. Use BONSITY right away after you remove it from the refrigerator.
- Do not freeze BONSITY. Do not use BONSITY if it has been frozen.
- Throw away the BONSITY delivery device after 28 days even if it has medicine in it (see the User Manual).
- Do not use BONSITY after the expiration date printed on the delivery device and packaging.
- Recap BONSITY when not in use to protect it from physical damage and light.

Keep BONSITY and all medicines out of the reach of children.

General information about the safe and effective use of BONSITY
Medicines are sometimes prescribed for purposes other than those listed in a Medication Guide. Do not use BONSITY for a condition for which it was not prescribed. Do not give BONSITY to other people, even if they have the same symptoms you have. It may harm them.
You can ask your pharmacist or healthcare provider for information about BONSITY that is written for healthcare professionals.

What are the ingredients in BONSITY?
Active ingredient: teriparatide
Inactive ingredients: glacial acetic acid, sodium acetate, mannitol, metacresol, and water for injection.

BONSITY® is a registered trademark of Pfenex, Inc.
For more information, go to www.bonsity.com or call Alvogen, Inc. at 1-866-770-3024.
Distributed by:
Alvogen, Inc.
Morristown, NJ 07960 USA

This Medication Guide has been approved by the U.S. Food and Drug Administration

Revised: 12/2024

PL852-00

PATIENT INFORMATION

User Manual

Storage Information

Always store the device in the refrigerator with the white cap on.
DO NOT store the device with a needle attached.
The device can be stored in the refrigerator after first use for 28 days.
Dispose device after 28 days of use.

DO NOT start the administration procedure until you have read the Medication Guide and this User Manual contained in your BONSITY carton thoroughly. Follow the instructions carefully whenever using the BONSITY device.
DO NOT share your BONSITY device or needles with anyone else. Infection or disease can be spread from one person to another.
DO NOT use the BONSITY device for more than 28 days. The BONSITY device contains 28 days of medicine. After 28 days of use dispose of this device even if it is not completely empty.
DO NOT inject more than one dose of BONSITY in the same day.
DO NOT attempt to transfer BONSITY from the device provided to syringe or any other device.

Prepare for Injection

1. Prepare Site and Remove the White Cap
A) Wash hands prior to use.
B) Prepare the injection site (thigh or abdomen) as recommended by your healthcare provider.
C) Remove the white cap by pulling it straight off of the device (Figure B).

2. Check Device, Device Label and Medication
A) Check the device.
DO NOT use the BONSITY device if it is damaged.
B) Check the label on the device.
DO NOT use if the device contains the incorrect medication or if the medication has expired (Figure C).
C) Check the medication cartridge. The liquid medication should be clear and colorless.
DO NOT use the medication if it is cloudy, colored, or has floating particles. (Figure C).

3. Attach New Needle
A) Peel off the paper tab (Figure D).
B) Push the needle straight onto medicine cartridge. Screw on needle clockwise until firmly attached (Figure E and Figure F).
DO NOT over-tighten the needle.

4. Remove Outer Needle Cover
Pull off large outer needle cover (Figure G), and save it for later (see Step 9).

5. Set Dose
Pull out the black injection button until it stops (Figure H).
Check to make sure red stripe shows. Additionally, the instruction window will show an arrow pointing towards the needle end of the device (Figure I).

Troubleshooting
If the device does not set fully or if you cannot pull back on the black injection button refer to Troubleshooting Problem E on the back page.

Administer Injection

6. Remove Inner Needle Cover
A) Pull off small inner needle protector and throw it away (Figure J).
B) CAUTION: The needle will be exposed.

7. Inject Dose
A) Gently hold a fold of skin on your thigh or abdomen and insert the needle straight into the folded skin (Figure K).
B) Press the black injection button down until it stops and hold (Figure L).
C) Hold it in and count to 5 slowly. You must wait until the count of 5 to make sure the full dose has been delivered (Figure M).
D) Remove the needle from the skin (Figure N). Once needle is removed from skin, take your thumb off the black injection button.

Note: You may not see the plunger moving. To confirm that your dose has been delivered, see Step 8.

After Injection

8. Confirm Dose
Check to make sure the black injection button is all the way down. The instruction window will show an arrow pointing towards the black button.
If the yellow shaft does not show, you have finished the injection steps the right way (Figure O).

Important
You should not see any of the yellow shaft. If you do and have already injected the medicine, do not inject yourself a second time in the same day.
Instead, you must reset the device.
Refer to Troubleshooting Problem A on the back page for more information.

9. Remove Needle and Dispose
A) Put the large outer needle cover on the needle by scooping it up and pressing it on (Figure P and Figure Q). Do not try to put the needle cover back on with your hands.
B) Unscrew the covered needle all the way by giving the large needle cover 3-5 counter-clockwise turns (Figure R).
Pull the needle straight off (Figure S).
C) Dispose of the needle into a puncture resistant container according to local regulations (Figure T). DO NOT reuse needle.

Disposal Information
For more information about how to correctly dispose of the needle refer to the Disposal Information section on the back page.

10. Recap Device and Store
A) Push white cap back on (Figure U).
B) Always store the device in the refrigerator with the white cap on right after use (Figure V).
DO NOT store the device with a needle attached.

Revised November 2024

See Reverse Side for More Information

Troubleshooting

Problem | Solution
A. The yellow shaft is still showing after I push in the black injection button. How do I reset my BONSITY delivery device? | To reset the BONSITY delivery device, follow the steps below: 1) If you have already injected, DO NOT inject yourself a second time on the same day. 2) Remove the needle and dispose in a sharps container according to local regulations. 3) Attach a new needle, pull off the large needle cover and save it. 4) Pull off the inner needle cover and throw away. 5) Point the needle down into an empty container. Push in the black injection button until it stops. Hold it in and slowly count to five. You may see a small stream or a drop of fluid. When you have finished, the black injection button should be all the way in. 6) If you still see the yellow shaft showing, contact Alvogen, Inc. (see Contact Information below and to the right) or your healthcare provider. 7) Remove the needle and dispose in a sharps container according to local regulations. Push the white cap back on, and put your BONSITY delivery device in the refrigerator. You can prevent this problem by always using a NEW needle for each injection, and by pushing the black injection button all the way in and slowly counting to five.
B. How can I tell if my BONSITY delivery device works? | The black injection button should be all the way in to show that the full dose of medicine has been injected from the BONSITY delivery device. Use a new needle every time you inject to be sure your BONSITY delivery device will work properly.
C. I see an air bubble in my BONSITY delivery device. | A small air bubble will not affect your dose and it will not harm you. You can continue to take your dose as usual.
D. I cannot get the needle off. | 1) Put the large needle cover on the needle. 2) Use the large needle cover to unscrew the needle. 3) Unscrew the needle all the way by giving the large needle cover 3 to 5 counter-clockwise turns. 4) If you still cannot get the needle off, ask someone to help you.
E. What should I do if I have difficulty pulling out the black injection button? | Change to a new BONSITY delivery device to take your dose as instructed by your healthcare provider. When the black injection button becomes hard to pull out, this means there is not enough medicine in your BONSITY delivery device for another dose. You may still see some medicine left in the cartridge.

Disposal Information

Put your used needles in a FDA-cleared sharps disposal container right away after use.

DO NOT throw away (dispose of) loose needles in your household trash.

If you do not have a FDA-cleared sharps disposal container, you may use a container that is:

- Made of a heavy-duty plastic
- Can be closed with a tight-fitting, puncture-resistant lid, without sharps being able to come out
- Upright and stable during use
- Leak-resistant
- Properly labeled to warn of hazardous waste inside the container

When your sharps disposal container is almost full, you will need to follow your community guidelines for the right way to dispose of your sharps disposal container. There may be state or local laws about how you should throw away used needles.

For more information about safe sharps disposal, and for specific information about sharps disposal in the state that you live in, go to the FDA's website at: http://www.fda.gov/safesharpsdisposal.

DO NOT dispose of your used sharps disposal container in your household trash unless your community guidelines permit this.

DO NOT recycle your used sharps disposal container.

Cleaning and Storage

Cleaning Your BONSITY Delivery Device

- Wipe the outside of the BONSITY delivery device with a damp cloth.
- Do not place the BONSITY delivery device in water, or wash or clean it with any liquid.

Storing Your BONSITY Delivery Device

- After each use, refrigerate the BONSITY delivery device right away. Read and follow the instructions in the Medication Guide section "How should I store BONSITY?".
- DO NOT store the BONSITY delivery device with a needle attached. Doing this may cause air bubbles to form in the medicine cartridge.
- Store the BONSITY delivery device with the white cap on.
- DO NOT freeze BONSITY. If the BONSITY delivery device has been frozen, throw the device away and use a new BONSITY delivery device. If the BONSITY delivery device has been left out of the refrigerator, do not throw the delivery device away. Place the delivery device back in the refrigerator and call Alvogen, Inc. (see Contact Information below).

Other Important Notes

- The BONSITY delivery device contains 28 days of medicine.
- Each device contains additional volume to allow troubleshooting of the device 2 times.
- DO NOT transfer BONSITY to a syringe. This may result in you taking the wrong dose of medicine.
- Read and follow the instructions in the User Manual so that you use your BONSITY delivery device the right way.
- Check the BONSITY delivery device label to make sure you have the right medicine and that it has not expired.
- DO NOT use the BONSITY delivery device if it looks damaged. Look at the BONSITY medicine in the cartridge. If the medicine is not clear and colorless, or if it has particles, do not use it. Call Alvogen, Inc. if you notice any of these (see Contact Information below).
- Use a new needle for each injection.
- During injection, you may hear one or more clicks - this is normal.
- The BONSITY delivery device is not recommended for use by the blind or by those who have vision problems without help from a person trained in the proper use of the device.
- Keep your BONSITY delivery device and needles out of the reach of children.

Disposal of Pen Needles and Delivery Device

Disposal of Pen Needles and the BONSITY Delivery Device

- Before throwing away the BONSITY delivery device, be sure to remove the pen needle.
- Throw away your BONSITY delivery device and used needles as instructed by your healthcare provider, local or state laws, or institutional policies.

Dispose of the BONSITY delivery device 28 days after first use. | 1st Use Date: __________ / __________ / _________ Throw Away After: _________ / ___________ / _________

Contact Information

If you have questions or need help with your BONSITY® delivery device, contact Alvogen, Inc. at 1-866-770-3024 or your healthcare provider. For more information about BONSITY, go to www.bonsity.com.

Distributed by: Alvogen, Inc.
Morristown, NJ 07960 USA

BONSITY® is a registered trademark of Pfenex Inc.

Revised: November 2024
IFU852-00

PRINCIPAL DISPLAY PANEL - Carton

Do NOT transfer contents to a syringe.

NDC 47781-852-89

ATTENTION PHARMACIST: Medication Guide (attached to Prescribing Information) and device User Manual for patient inside carton.

BONSITY®
teriparatide injection
560 mcg/2.24 mL (250 mcg/mL)

20 mcg per dose (given once daily subcutaneously)

For Single-Patient-Use Only

Rx Only